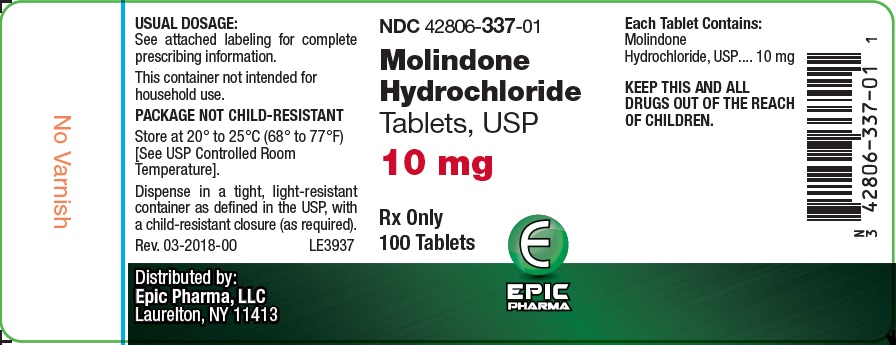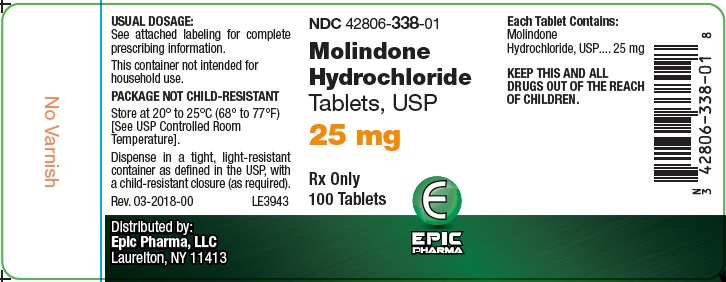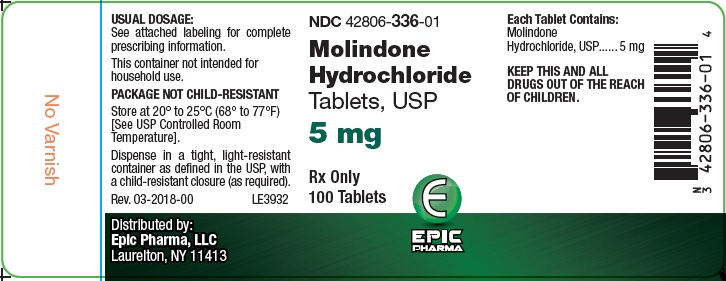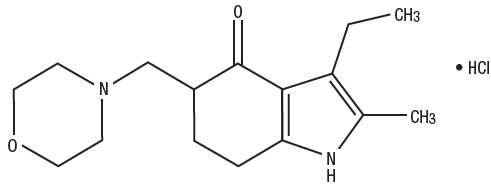 DRUG LABEL: Molindone Hydrochloride
NDC: 42806-336 | Form: TABLET
Manufacturer: EPIC PHARMA, LLC
Category: prescription | Type: HUMAN PRESCRIPTION DRUG LABEL
Date: 20251217

ACTIVE INGREDIENTS: MOLINDONE HYDROCHLORIDE 5 mg/1 1
INACTIVE INGREDIENTS: ALGINIC ACID; CALCIUM SULFATE, UNSPECIFIED FORM; SILICON DIOXIDE; LACTOSE MONOHYDRATE; MAGNESIUM STEARATE; MICROCRYSTALLINE CELLULOSE; POVIDONE, UNSPECIFIED; SODIUM STARCH GLYCOLATE TYPE A POTATO; FD&C YELLOW NO. 6

Molindone Hydrochloride Tablets

WARNING

Increased Mortality in Elderly Patients with Dementia-Related Psychosis – Elderly patients with dementia-related psychosis treated with antipsychotic drugs are at an increased risk of death. Analyses of seventeen placebo-controlled trials (modal duration of 10 weeks), largely in patients taking atypical antipsychotic drugs, revealed a risk of death in drug-treated patients of between 1.6 to 1.7 times the risk of death in placebo-treated patients. Over the course of a typical 10-week controlled trial, the rate of death in drug-treated patients was about 4.5%, compared to a rate of about 2.6% in the placebo group. Although the causes of death were varied, most of the deaths appeared to be either cardiovascular (e.g., heart failure, sudden death) or infectious (e.g., pneumonia) in nature. Observational studies suggest that, similar to atypical antipsychotic drugs, treatment with conventional antipsychotic drugs may increase mortality. The extent to which the findings of increased mortality in observational studies may be attributed to the antipsychotic drug as opposed to some characteristic(s) of the patients is not clear. Molindone Hydrochloride Tablets, USP are not approved for the treatment of patients with dementia-related psychosis (see WARNINGS).

DESCRIPTION

Molindone Hydrochloride is a dihydroindolone compound which is not structurally related to the phenothiazines, the butyrophenones or the thioxanthenes.

Molindone Hydrochloride is 3-ethyl-6, 7-dihydro-2-methyl-5-(morpholinomethyl) indol-4(5H)-one hydrochloride. It is a white to off-white or pale-pink crystalline powder, freely soluble in water and alcohol.

Molindone Hydrochloride Tablets, USP contain the following inactive ingredients: alginic acid, calcium sulfate, colloidal silicon dioxide, lactose monohydrate, magnesium stearate, microcrystalline cellulose, povidone and sodium starch glycolate.

Colors: 5 mg contains FD&C Yellow #6 Aluminum Lake

10 mg contains FD&C Blue #2 Aluminum Lake
25 mg contains FD&C Blue #2 Aluminum Lake, FD&C Yellow #6, Aluminum Lake and D&C Yellow #10 Aluminum Lake

Molindone Hydrochloride is represented by the following structural formula:

The empirical formula is C16H24N2O2•HCl representing a molecular weight of 312.83.

CLINICAL PHARMACOLOGY

Molindone Hydrochloride has a pharmacological profile in laboratory animals which predominantly resembles that of other antipsychotic agents causing reduction of spontaneous locomotion and aggressiveness, suppression of a conditioned response and antagonism of the bizarre stereotyped behavior and hyperactivity induced by amphetamines. In addition, Molindone Hydrochloride antagonizes the depression caused by the tranquilizing agent tetrabenazine.

In human clinical studies an antipsychotic effect is achieved in the absence of muscle relaxing or incoordinating effects. Based on EEG studies, Molindone Hydrochloride exerts its effect on the ascending reticular activating system.

Human metabolic studies show Molindone Hydrochloride Tablets to be rapidly absorbed and metabolized when given orally. Unmetabolized drug reached a peak blood level at 1.5 hours. Pharmacological effect from a single oral dose persists for 24 to 36 hours. There are 36 recognized metabolites with less than 2 to 3% unmetabolized Molindone Hydrochloride Tablets being excreted in urine and feces.

INDICATIONS AND USAGE

Molindone Hydrochloride Tablets, USP are indicated for the management of schizophrenia. The efficacy of Molindone Hydrochloride Tablets, USP in schizophrenia was established in clinical studies which enrolled newly hospitalized and chronically hospitalized, acutely ill, schizophrenic patients as subjects.

CONTRAINDICATIONS

Molindone Hydrochloride Tablets are contraindicated in severe central nervous system depression (alcohol, barbiturates, narcotics, etc.) or comatose states, and in patients with known hypersensitivity to the drug.

WARNINGS

Increased Mortality in Elderly Patients with Dementia-Related Psychosis — Elderly patients with dementia-related psychosis treated with antipsychotic drugs are at an increased risk of death.

Molindone Hydrochloride Tablets are not approved for the treatment of patients with dementia-related psychosis (see BOXED WARNING).

Tardive Dyskinesia

Tardive dyskinesia, a syndrome consisting of potentially irreversible, involuntary, dyskinetic movements may develop in patients treated with antipsychotic drugs. Although the prevalence of the syndrome appears to be highest among the elderly, especially elderly women, it is impossible to rely upon prevalence estimates to predict, at the inception of antipsychotic treatment, which patients are likely to develop the syndrome. Whether antipsychotic drug products differ in their potential to cause tardive dyskinesia is unknown.

Both the risk of developing the syndrome and the likelihood that it will become irreversible are believed to increase as the duration of treatment and the total cumulative dose of antipsychotic drugs administered to the patient increase. However, the syndrome can develop, although much less commonly, after relatively brief treatment periods at low doses.

There is no known treatment for established cases of tardive dyskinesia, although the syndrome may remit, partially or completely, if antipsychotic treatment is withdrawn. Antipsychotic treatment, itself, however, may suppress (or partially suppress) the signs and symptoms of the syndrome and thereby may possibly mask the underlying disease process. The effect that symptomatic suppression has upon the long-term course of the syndrome is unknown.

Given these considerations, antipsychotics should be prescribed in a manner that is most likely to minimize the occurrence of tardive dyskinesia. Chronic antipsychotic treatment should generally be reserved for patients who suffer from a chronic illness that, 1) is known to respond to antipsychotic drugs, and 2) for whom alternative, equally effective, but potentially less harmful treatments are not available or appropriate. In patients who do require chronic treatment, the smallest dose and the shortest duration of treatment producing a satisfactory clinical response should be sought. The need for continued treatment should be reassessed periodically.

If signs and symptoms of tardive dyskinesia appear in a patient on antipsychotics, drug discontinuation should be considered. However, some patients may require treatment despite the presence of the syndrome.

(For further information about the description of tardive dyskinesia and its clinical detection, please refer to the section on ADVERSE REACTIONS.)

Falls

Molindone Hydrochloride may cause somnolence, postural hypotension, motor and sensory instability, which may lead to falls and, consequently, fractures or other injuries. For patients with diseases, conditions, or medications that could exacerbate these effects, complete fall risk assessments when initiating antipsychotic treatment and recurrently for patients on long-term antipsychotic therapy.

Neuroleptic Malignant Syndrome (NMS)

A potentially fatal symptom complex sometimes referred to as Neuroleptic Malignant Syndrome (NMS) has been reported in association with antipsychotic drugs. Clinical manifestations of NMS are hyperpyrexia, muscle rigidity, altered mental status and evidence of autonomic instability (irregular pulse or blood pressure, tachycardia, diaphoresis, and cardiac dysrhythmias).

The diagnostic evaluation of patients with this syndrome is complicated. In arriving at a diagnosis, it is important to identify cases where the clinical presentation includes both serious medical illness (e.g., pneumonia, systemic infection, etc.) and untreated or inadequately treated extrapyramidal signs and symptoms (EPS). Other important considerations in the differential diagnosis include central anticholinergic toxicity, heat stroke, drug fever and primary central nervous system (CNS) pathology.

The management of NMS should include, 1) immediate discontinuation of antipsychotic drugs and other drugs not essential to concurrent therapy, 2) intensive symptomatic treatment and medical monitoring, and 3) treatment of any concomitant serious medical problems for which specific treatments are available. There is no general agreement about specific pharmacological treatment regimens for uncomplicated NMS.

If a patient requires antipsychotic drug treatment after recovery from NMS, the potential reintroduction of drug therapy should be carefully considered. The patient should be carefully monitored, since recurrences of NMS have been reported.

PRECAUTIONS

General

Some patients receiving Molindone Hydrochloride may note drowsiness initially and they should be advised against activities requiring mental alertness until their response to the drug has been established.

Increased activity has been noted in patients receiving Molindone Hydrochloride. Caution should be exercised where increased activity may be harmful.

Molindone Hydrochloride does not lower the seizure threshold in experimental animals to the degree noted with more sedating antipsychotic drugs. However, in humans convulsive seizures have been reported in a few instances.

The physician should be aware that this tablet preparation contains calcium sulfate as an excipient and that calcium ions may interfere with the absorption of preparations containing phenytoin sodium and tetracyclines.

Molindone Hydrochloride has an antiemetic effect in animals. A similar effect may occur in humans and may obscure signs of intestinal obstruction or brain tumor.

Antipsychotic drugs elevate prolactin levels; the elevation persists during chronic administration. Tissue culture experiments indicate that approximately one-third of human breast cancers are prolactin dependent in vitro, a factor of potential importance if the prescription of these drugs is contemplated in a patient with a previously detected breast cancer. Although disturbances such as galactorrhea, amenorrhea, gynecomastia, and impotence have been reported, the clinical significance of elevated serum prolactin levels is unknown for most patients. An increase in mammary neoplasms has been found in rodents after chronic administration of antipsychotic drugs. Some epidemiologic studies have indicated a potential association between chronic administration of prolactin- increasing antipsychotics and breast cancer.

Molindone Hydrochloride has not been shown effective in the management of behavioral complications in patients with mental retardation.

Leukopenia, Neutropenia and Agranulocytosis

Some patients receiving Molindone Hydrochloride may note drowsiness initially and they should be advised against activities requiring mental alertness until their response to the drug has been established.

Increased activity has been noted in patients receiving Molindone Hydrochloride. Caution should be exercised where increased activity may be harmful.

Molindone Hydrochloride does not lower the seizure threshold in experimental animals to the degree noted with more sedating antipsychotic drugs. However, in humans convulsive seizures have been reported in a few instances.

The physician should be aware that this tablet preparation contains calcium sulfate as an excipient and that calcium ions may interfere with the absorption of preparations containing phenytoin sodium and tetracyclines.

Molindone Hydrochloride has an antiemetic effect in animals. A similar effect may occur in humans and may obscure signs of intestinal obstruction or brain tumor.

Antipsychotic drugs elevate prolactin levels; the elevation persists during chronic administration. Tissue culture experiments indicate that approximately one-third of human breast cancers are prolactin dependent in vitro, a factor of potential importance if the prescription of these drugs is contemplated in a patient with a previously detected breast cancer. Although disturbances such as galactorrhea, amenorrhea, gynecomastia, and impotence have been reported, the clinical significance of elevated serum prolactin levels is unknown for most patients. An increase in mammary neoplasms has been found in rodents after chronic administration of antipsychotic drugs. Neither clinical studies nor epidemiologic studies conducted to date, however, have shown an association between chronic administration of these drugs and mammary tumorigenesis; the available evidence is considered too limited to be conclusive at this time. Some epidemiologic studies have indicated a potential association between chronic administration of prolactin-increasing antipsychotics and breast cancer. Published epidemiologic studies have shown inconsistent results when exploring the association between hyperprolactinemia and breast cancer.

Molindone Hydrochloride has not been shown effective in the management of behavioral complications in patients with mental retardation.

Leukopenia, Neutropenia and Agranulocytosis

Class Effect: In clinical trial and/or postmarketing experience, events of leukopenia/neutropenia and agranulocytosis have been reported temporally related to antipsychotic agents.

Possible risk factors for leukopenia/neutropenia include preexisting low white blood cell count (WBC) and history of drug induced leukopenia/neutropenia. Patients with a history of a clinically significant low WBC or drug induced leukopenia/neutropenia should have their complete blood count (CBC) monitored frequently during the first few months of therapy and discontinuation of Molindone Hydrochloride should be considered at the first sign of a clinically significant decline in WBC in the absence of other causative factors.

Patients with clinically significant neutropenia should be carefully monitored for fever or other symptoms or signs of infection and treated promptly if such symptoms or signs occur. Patients with severe neutropenia (absolute neutrophil count <1000/mm3) should discontinue Molindone Hydrochloride and have their WBC followed until recovery.

Drug Interactions

Potentiation of drugs administered concurrently with Molindone Hydrochloride has not been reported. Additionally, animal studies have not shown increased toxicity when Molindone Hydrochloride is given concurrently with representative members of three classes of drugs (i.e., barbiturates, chloral hydrate and antiparkinson drugs).

Pregnancy

Studies in pregnant patients have not been carried out. Reproduction studies have been performed in the following animals:

Pregnant Rats oral dose—

no adverse effect 20 mg/kg/day - 10 days

no adverse effect 40 mg/kg/day - 10 days

Pregnant Mice oral dose—

slight increase resorptions 20 mg/kg/day - 10 days

slight increase resorptions 40 mg/kg/day - 10 days

Pregnant Rabbits oral dose—

no adverse effect 5 mg/kg/day - 12 days

no adverse effect 10 mg/kg/day - 12 days

no adverse effect 20 mg/kg/day - 12 days

Animal reproductive studies have not demonstrated a teratogenic potential. The anticipated benefits must be weighed against the unknown risks to the fetus if used in pregnant patients.

Non-teratogenic Effects

Neonates exposed to antipsychotic drugs, during the third trimester of pregnancy are at risk for extrapyramidal and/or withdrawal symptoms following delivery. There have been reports of agitation, hypertonia, hypotonia, tremor, somnolence, respiratory distress and feeding disorder in these neonates. These complications have varied in severity; while in some cases symptoms have been self-limited, in other cases neonates have required intensive care unit support and prolonged hospitalization.

Molindone Hydrochloride should be used during pregnancy only if the potential benefit justifies the potential risk to the fetus.

Nursing Mothers

Data are not available on the content of Molindone Hydrochloride in the milk of nursing mothers.

Pediatric Use

Use of Molindone Hydrochloride in pediatric patients below the age of twelve years is not recommended because safe and effective conditions for its usage have not been established.

ADVERSE REACTIONS

CNS Effects

The most frequently occurring effect is initial drowsiness that generally subsides with continued usage of the drug or lowering of the dose.

Noted less frequently were depression, hyperactivity and euphoria.

Extrapyramidal Symptoms

Extrapyramidal symptoms noted below may occur in susceptible individuals and are usually reversible with appropriate management.

Akathisia

Motor restlessness may occur early.

Parkinson Syndrome

Akinesia, characterized by rigidity, immobility and reduction of voluntary movements and tremor, have been observed. Occurrence is less frequent than akathisia.

Dystonia

Class effect: Symptoms of dystonia, prolonged abnormal contractions of muscle groups, may occur in susceptible individuals during the first few days of treatment. Dystonic symptoms include: spasm of the neck muscles, sometimes progressing to tightness of the throat, swallowing difficulty, difficulty breathing, and/or protrusion of the tongue. While these symptoms can occur at low doses, they occur more frequently and with greater severity with high potency and at higher doses of first generation antipsychotic drugs. An elevated risk of acute dystonia is observed in males and younger age groups.

Tardive Dyskinesia

Antipsychotic drugs are known to cause a syndrome of dyskinetic movements commonly referred to as tardive dyskinesia. The movements may appear during treatment or upon withdrawal of treatment and may be either reversible or irreversible (i.e., persistent) upon cessation of further antipsychotic administration.

The syndrome is known to have a variable latency for development and the duration of the latency cannot be determined reliably. It is thus wise to assume that any antipsychotic agent has the capacity to induce the syndrome and act accordingly until sufficient data has been collected to settle the issue definitively for a specific drug product. In the case of antipsychotics known to produce the irreversible syndrome, the following has been observed.

Tardive dyskinesia has appeared in some patients on long-term therapy and has also appeared after drug therapy has been discontinued. The risk appears to be greater in elderly patients on high-dose therapy, especially females. The symptoms are persistent and in some patients appear to be irreversible. The syndrome is characterized by rhythmical involuntary movements of the tongue, face, mouth or jaw (e.g., protrusion of tongue, puffing of cheeks, puckering of mouth, chewing movements). There may be involuntary movements of extremities.

There is no known effective treatment of tardive dyskinesia; antiparkinsonism agents usually do not alleviate the symptoms of this syndrome. It is suggested that all antipsychotic agents be discontinued if these symptoms appear. Should it be necessary to reinstitute treatment, or increase the dosage of the agent, or switch to a different antipsychotic agent, the syndrome may be masked. It has been reported that fine vermicular movements of the tongue may be an early sign of the syndrome and if the medication is stopped at that time the syndrome may not develop (See WARNINGS).

Autonomic Nervous System

Occasionally blurring of vision, tachycardia, nausea, dry mouth and salivation have been reported. Urinary retention and constipation may occur particularly if anticholinergic drugs are used to treat extrapyramidal symptoms. One patient being treated with Molindone Hydrochloride experienced priapism which required surgical intervention, apparently resulting in residual impairment of erectile function.

Laboratory Tests

There have been rare reports of leucopenia and leucocytosis. If such reactions occur, treatment with Molindone Hydrochloride may continue if clinical symptoms are absent. Alterations of blood glucose, B.U.N., and red blood cells have not been considered clinically significant.

Metabolic and Endocrine Effects

Alteration of thyroid function has not been significant. Amenorrhea has been reported infrequently. Resumption of menses in previously amenorrheic women has been reported. Initially heavy menses may occur. Galactorrhea and gynecomastia have been reported infrequently. Increase in libido has been noted in some patients. Impotence has not been reported. Although both weight gain and weight loss have been in the direction of normal or ideal weight, excessive weight gain has not occurred with Molindone Hydrochloride.

Hepatic Effects

There have been rare reports of clinically significant alterations in liver function in association with Molindone Hydrochloride use.

Cardiovascular

Rare, transient, non-specific T wave changes have been reported on E.K.G. Association with a clinical syndrome has not been established. Rarely has significant hypotension been reported.

Ophthalmological

Lens opacities and pigmentary retinopathy have not been reported where patients have received Molindone Hydrochloride. In some patients, phenothiazine induced lenticular opacities have resolved following discontinuation of the phenothiazine while continuing therapy with Molindone Hydrochloride.

Skin

Early, non-specific skin rash, probably of allergic origin, has occasionally been reported. Skin pigmentation has not been seen with Molindone Hydrochloride usage alone.

Molindone Hydrochloride has certain pharmacological similarities to other antipsychotic agents. Because adverse reactions are often extensions of the pharmacological activity of a drug, all of the known pharmacological effects associated with other antipsychotic drugs should be kept in mind when Molindone Hydrochloride is used. Upon abrupt withdrawal after prolonged high dosage an abstinence syndrome has not been noted.

OVERDOSAGE

Symptomatic, supportive therapy should be the rule.

Gastric lavage is indicated for the reduction of absorption of Molindone Hydrochloride which is freely soluble in water.

Since the adsorption of Molindone Hydrochloride by activated charcoal has not been determined, the use of this antidote must be considered of theoretical value.

Emesis in a comatose patient is contraindicated. Additionally, while the emetic effect of apomorphine is blocked by Molindone Hydrochloride in animals, this blocking effect has not been determined in humans.

A significant increase in the rate of removal of unmetabolized Molindone Hydrochloride from the body by forced diuresis, peritoneal or renal dialysis would not be expected. (Only 2% of a single ingested dose of Molindone Hydrochloride is excreted unmetabolized in the urine). However, poor response of the patient may justify use of these procedures.

While the use of laxatives or enemas might be based on general principles, the amount of unmetabolized Molindone Hydrochloride in feces is less than 1%. Extrapyramidal symptoms have responded to the use of Diphenhydramine (Benadryl®)*, Amantadine HCl (Symmetrel®)† and the synthetic anticholinergic antiparkinson agents, (i.e., Artane®‡, Cogentin®§, Akineton®¶).

DOSAGE AND ADMINISTRATION

Initial and maintenance doses of Molindone Hydrochloride Tablets should be individualized.

Initial Dosage Schedule

The usual starting dosage is 50 to 75 mg/day.

—Increase to 100 mg/day in 3 or 4 days.

—Based on severity of symptomatology, dosage may be titrated up or down depending on individual patient response.

—An increase to 225 mg/day may be required in patients with severe symptomatology.

Elderly and debilitated patients should be started on lower dosage.

Maintenance Dosage Schedule

1. Mild-5 mg to 15 mg three or four times a day.
2. Moderate-10 mg to 25 mg three or four times a day.

Severe-225 mg/day may be required.

HOW SUPPLIED

Molindone Hydrochloride Tablets USP, 5 mg are light orange to orange, oval-shaped tablets, debossed "Є336" on one side and plain on the other side. They are supplied as follows:

Bottles of 100 NDC 42806-336-01

Molindone Hydrochloride Tablets USP, 10 mg are light blue to blue, oval-shaped tablets, debossed "Є337" on one side and plain on the other side. They are supplied as follows:

Bottles of 100 NDC 42806-337-01

Molindone Hydrochloride Tablets USP, 25 mg are light green to green, oval-shaped tablet, debossed "Є338" on one side and bisect on the other side. They are supplied as follows:

Bottles of 100 NDC 42806-338-01

Store at 20° to 25°C (68° to 77°F) [See USP Controlled Room Temperature].

Dispense in a tight, light-resistant container as defined in the USP, with a child-resistant closure (as required).

KEEP TIGHTLY CLOSED

*Benadryl is a registered trademark of Warner-Lambert.

†Symmetrel is a registered trademark of Endo Pharmaceuticals Inc.

‡Artane is a registered trademark of Lederle Laboratories.

§Cogentin is a registered trademark of Merck & Co., Inc.

¶Akineton is a registered trademark of Knoll Laboratories.

Distributed by:

Epic Pharma, LLC

Laurelton NY, 11413

Rev. 11-2024-00

MF336REV11/24

OE2798